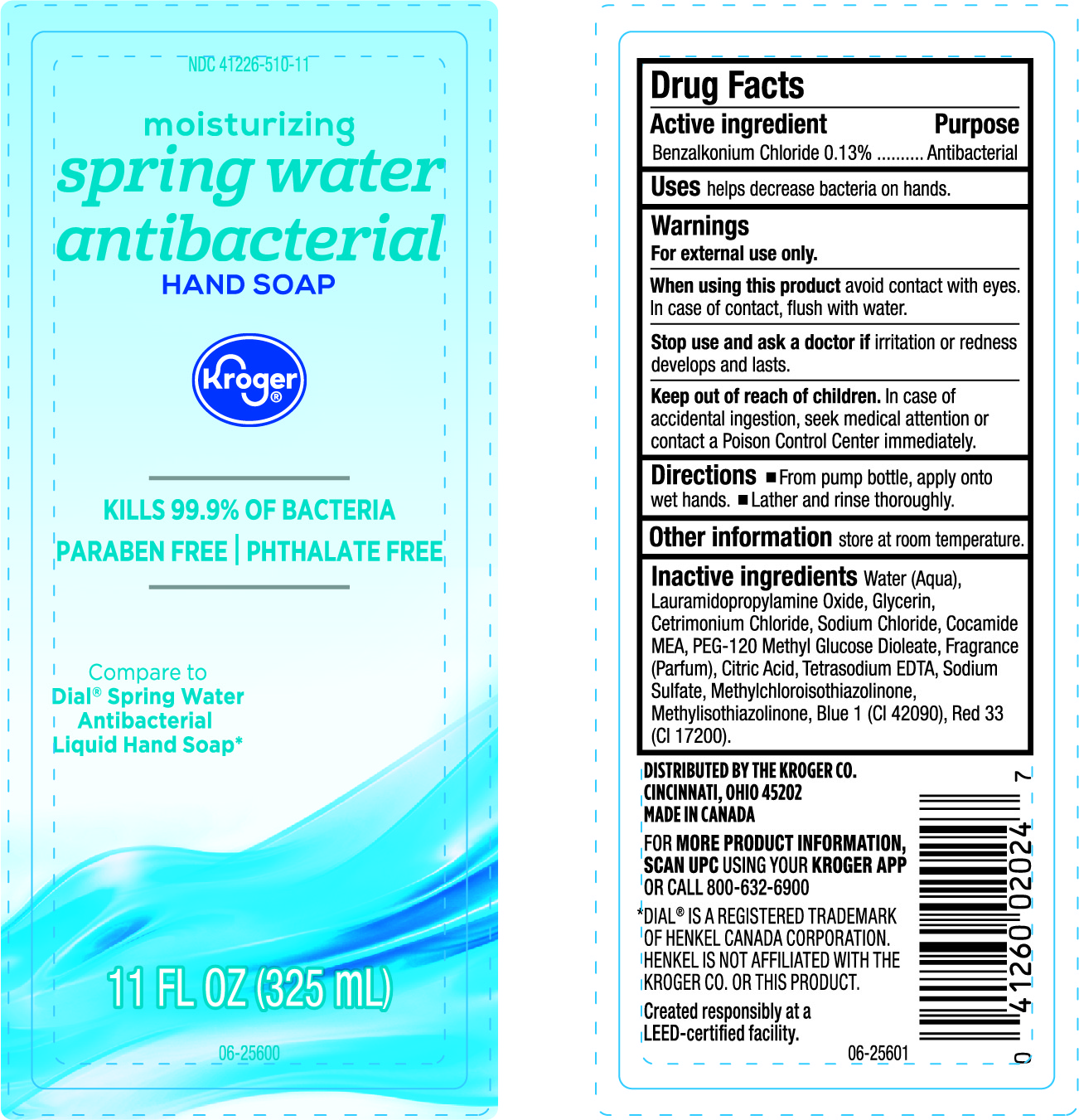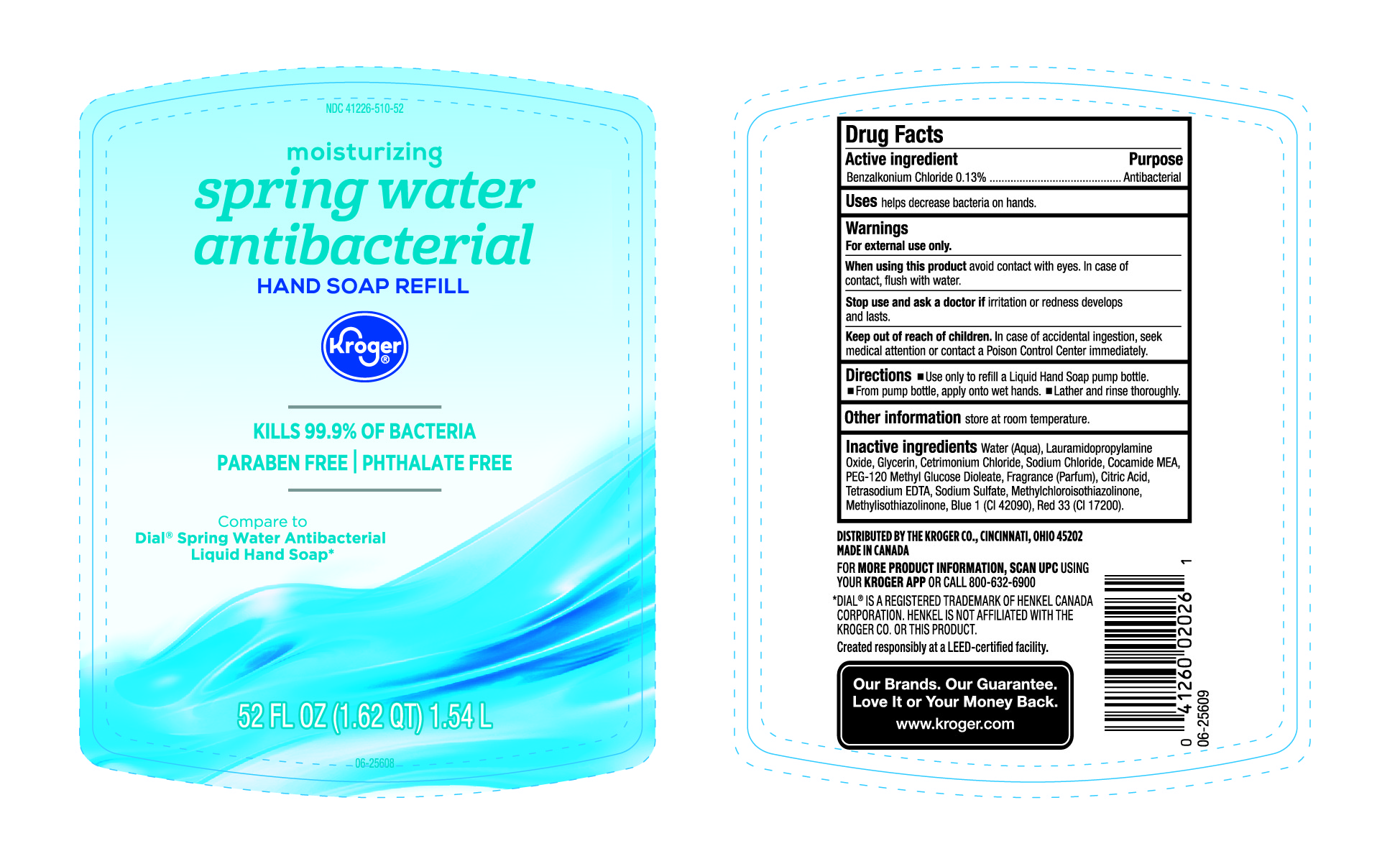 DRUG LABEL: Kroger Springwater Antibacterial
NDC: 41226-510 | Form: LIQUID
Manufacturer: Kroger Company
Category: otc | Type: HUMAN OTC DRUG LABEL
Date: 20250206

ACTIVE INGREDIENTS: BENZALKONIUM CHLORIDE 130 mg/100 mL
INACTIVE INGREDIENTS: WATER; METHYLCHLOROISOTHIAZOLINONE; FD&C BLUE NO. 1; EDETATE SODIUM; FRAGRANCE CLEAN ORC0600327; GLYCERIN; CETRIMONIUM CHLORIDE; SODIUM CHLORIDE; LAURAMIDOPROPYLAMINE OXIDE; COCO MONOETHANOLAMIDE; CITRIC ACID MONOHYDRATE; PEG-120 METHYL GLUCOSE DIOLEATE; SODIUM SULFATE; METHYLISOTHIAZOLINONE; D&C RED NO. 33

NDC-41226-510, Kroger Moisturizing spring water antibacterial Hand Soap

Active Ingredient

Benzalkonium Chloride 0.13%

Purpose

Antibacterial

Uses

Helps decrease bacteria on hands.

Warnings

For external use only.

When using the product

Avoid contact with eyes. In case of Contact, Flush with Water.

Keep out of reach of children.

In case of accidental ingestion, seek medical attention or contact a Poison Control Center immediately.

Directions

- From pump bottle, apply onto wet hands.
- Lather and rinse thoroughly.

Other Information

Store at room temperature.

Inactive Ingredients

Water (Aqua), Lauramidopropylamine Oxide, Glycerin, Cetrimonium Chloride, Sodium Chloride, Cocamide MEA, PEG-120 Methyl Glucose Dioleate, Fragrance (Parfum), Citric Acid, Tetrasodium EDTA, Sodium Sulfate, Methylchloroisothiazolinone, Methylisothiazolinone, Blue 1 (CI42090), Red 33 (CI 17200).